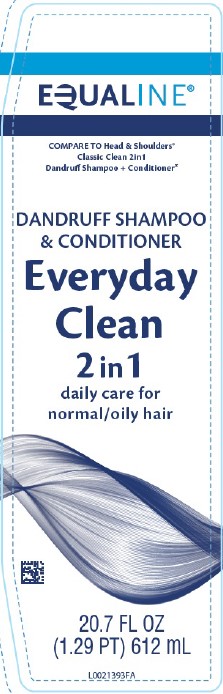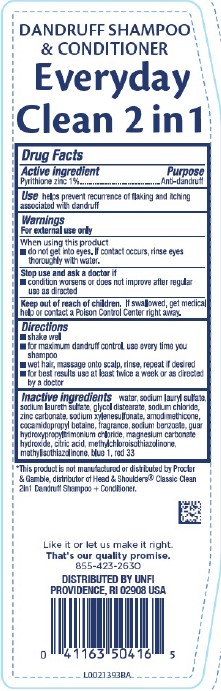 DRUG LABEL: Dandruff
NDC: 41163-024 | Form: LOTION/SHAMPOO
Manufacturer: United Natural Foods, Inc. dba UNFI
Category: otc | Type: HUMAN OTC DRUG LABEL
Date: 20260217

ACTIVE INGREDIENTS: PYRITHIONE ZINC 10 mg/1 mL
INACTIVE INGREDIENTS: FD&C BLUE NO. 1; D&C RED NO. 33; WATER; SODIUM LAURYL SULFATE; SODIUM LAURETH SULFATE; GLYCOL DISTEARATE; SODIUM CHLORIDE; ZINC CARBONATE; SODIUM XYLENESULFONATE; AMODIMETHICONE (800 CST); COCAMIDOPROPYL BETAINE; SODIUM BENZOATE; GUAR HYDROXYPROPYLTRIMONIUM CHLORIDE (1.7 SUBSTITUENTS PER SACCHARIDE); MAGNESIUM CARBONATE HYDROXIDE; CITRIC ACID MONOHYDRATE; METHYLCHLOROISOTHIAZOLINONE; METHYLISOTHIAZOLINONE

Equaline 311.007/311AK-AN
Dandruff Shampoo, Everyday Clean 2 in 1

Claims

DANDRUFF SHAMPOO & CONDITIONER

Everyday

Clean 2 in 1

Active ingredient

Pyrithione zinc 1%

Purpose

Anti-dandruff

Use

helps prevent recurrence of flaking and itching associated with dandruff

Warnings

For external use only

When using this product

- do not get into eyes. If contact occurs, rinse eyes thoroughly with water

Stop use and ask a doctor if

- condition worsens or does not improve after regular use as directed

Keep out of reach of children

if swallowed, get medical help or contact a Poison Control Center right away.

Directions

- shake well
- for maximum dandruff control, use every time you shampoo
- wet hair, massage onto scalp, rinse, repeat if desired
- for best results use at least twice a week or as directed by a doctor

inactive ingredients

water, sodium lauryl sulfate, sodium laureth sulfate, glycol distearate, sodium chloride, zinc carbonate, sodium xylenesulfonate, amodimethicone, cocamidopropyl betaine, fragrance, sodium benzoate, guar hydroxypropyltrimonium chloride, magnesium carbonate hydroxide, citric acid, methylchloroisothiazolinone, methylisothiazolinone, blue 1, red 33

Disclaimer

*This product is not manufactured or distributed by Procter & Gamble, the distributor of Head & Shoulders® Classic clean 2in1 Dandruff Shampoo + Conditioner.

Adverse Reactions

Like it or let us make it right.

That's our quality promise.

855-423-2630

DISTRIBUTED BY UNFI

PROVIDENCE, RI 02908 USA

principal display panel

EQUALINE®

COMPARE TO Head & Shoulders®Classic Clean 2in1 Dandruff Shampoo + Conditioner*

DANDRUFF SHAMPOO & CONDITIONER

Everyday Clean

2 in 1

daily care for normal/oily hair

20.7 FL OZ (1.29 PT) 612 mL